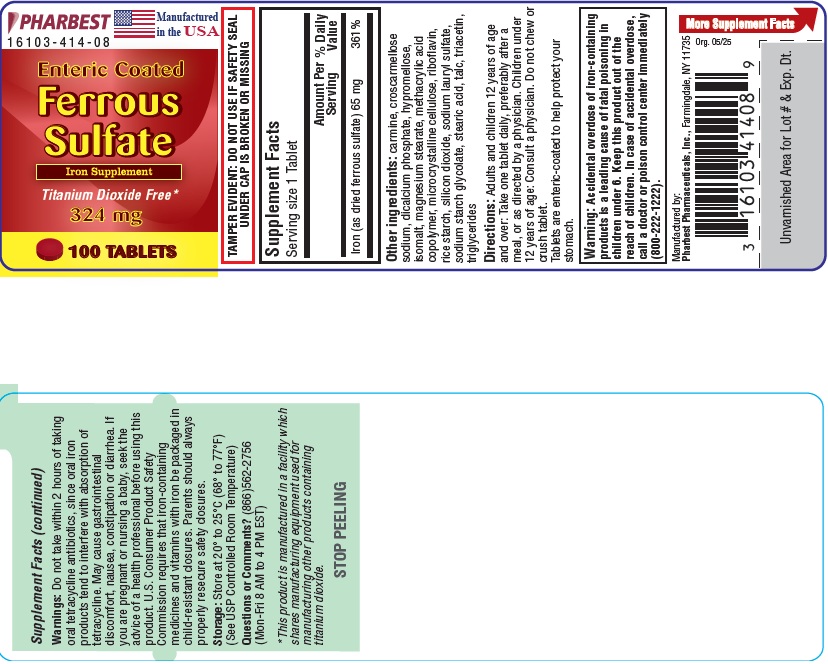 DRUG LABEL: Enteric Coated Ferrous Sulfate
NDC: 16103-414 | Form: TABLET, DELAYED RELEASE
Manufacturer: Pharbest Pharmaceuticals, Inc.
Category: other | Type: DIETARY SUPPLEMENT
Date: 20250619

ACTIVE INGREDIENTS: FERROUS SULFATE 65 mg/1 1
INACTIVE INGREDIENTS: CARMINIC ACID; CROSCARMELLOSE SODIUM; DIBASIC CALCIUM PHOSPHATE DIHYDRATE; HYPROMELLOSE, UNSPECIFIED; ISOMALT; MAGNESIUM STEARATE; METHACRYLIC ACID - METHYL METHACRYLATE COPOLYMER (1:1); MICROCRYSTALLINE CELLULOSE 102; RIBOFLAVIN; STARCH, RICE; SILICON DIOXIDE; SODIUM LAURYL SULFATE; SODIUM STARCH GLYCOLATE TYPE A; STEARIC ACID; TALC; TRIACETIN; MEDIUM-CHAIN TRIGLYCERIDES

Enteric Coated Ferrous Sulfate Tablet

STATEMENT OF IDENTITY

Supplement Facts
Serving Size: 1 Tablet
Amount Per Serving | % Daily Value
Iron (as dried ferrous sulfate) 65 mg | 361%

Other ingredients: carmine, croscarmellose sodium, dicalcium phosphate, hypromellose, isomalt, magnesium stearate, methacrylic acid copolymer, microcrystalline cellulose, riboflavin, rice starch, silicon dioxide, sodium lauryl sulfate, sodium starch glycolate, stearic acid, talc, triacetin, triglycerides

DOSAGE AND ADMINISTRATION

Directions: Adults and children 12 years of age and over: Take one tablet daily, preferably after a meal, or as directed by a physician. Children under 12 years of age: Consult a physician. Do not chew or crush tablet.

Tablets are enteric-coated to help protect your stomach.

SAFE HANDLING WARNING

Warning: Accidental overdose of iron-containing products is a leading cause of fatal poisoning in children under 6. Keep this product out of reach of children. In case of accidental overdose, call a doctor or poison control center immediately (800-222-1222).

WARNINGS

Warnings: Do not take within 2 hours of taking oral tetracycline antibiotics, since oral iron products tend to interfere with absorption of tetracycline. May cause gastrointestinal discomfort, nausea, constipation or diarrhea. If you are pregnant or nursing a baby, seek advice of a health professional before using this product. U.S. Consumer Product Safety Commission requires that iron-containing medicine and vitamins with iron be packaged in child-resistant closures. Parents should always use properly re-secure safety closures.

SAFE HANDLING WARNING

Storage: Store at 20° - 25°C (68° - 77°F) (see USP Controlled Room Temperature)

Questions or Comments? (866)562-2756 (Mon-Fri 8 AM to 4 PM EST)

HEALTH CLAIM

†This product is manufactured in a facility which shares manufacturing equipment used for manufacturing other product containing titanium dioxide.

HEALTH CLAIM

TAMPER EVIDENT: DO NOT USE IF SAFETY SEAL UNDER CAP IS BROKEN OR MISSING

HEALTH CLAIM

Manufactured by:
Pharbest Pharmaceuticals, Inc. Farmingdale, NY 11735

Org. 05/25

More Supplement Facts

PACKAGE LABEL

PHARBEST

Manufactured in the USA

16103-414-08

Enteric Coated

Ferrous Sulfate

Iron Supplement

Titanium Dioxide Free†

324 mg

100 Tablets